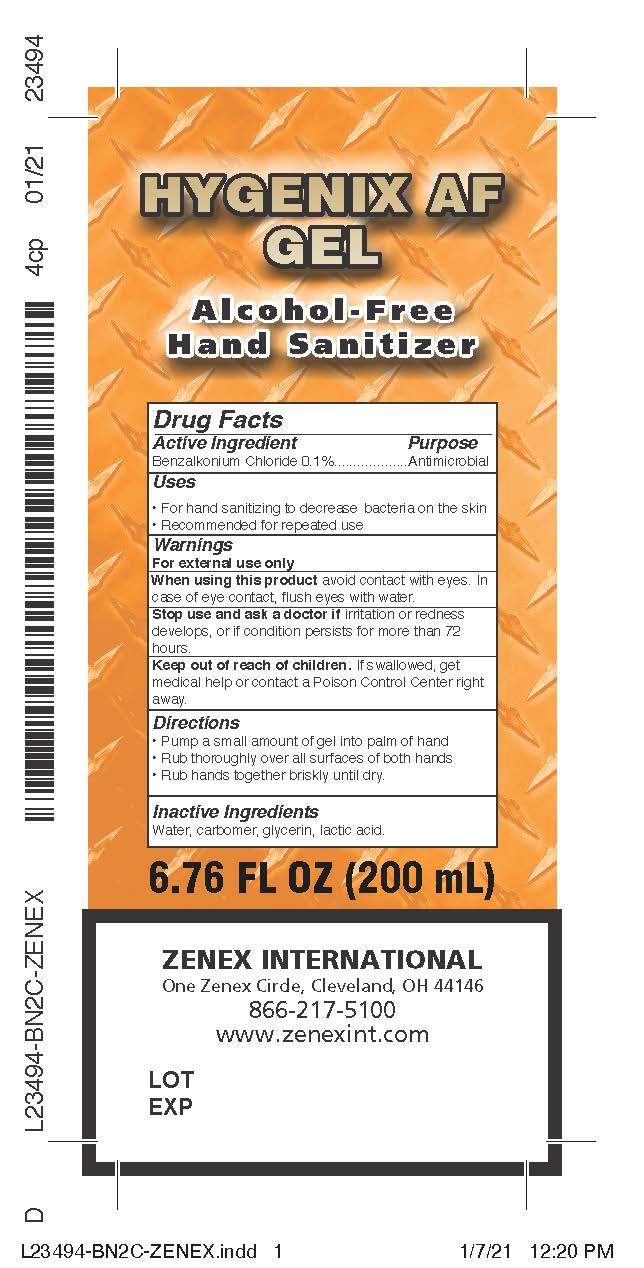 DRUG LABEL: Hygenix AF Gel
NDC: 74146-244 | Form: GEL
Manufacturer: GM Industrial, Inc.
Category: otc | Type: HUMAN OTC DRUG LABEL
Date: 20211005

ACTIVE INGREDIENTS: BENZALKONIUM CHLORIDE 1 mg/1 mL
INACTIVE INGREDIENTS: LACTIC ACID; CARBOMER HOMOPOLYMER, UNSPECIFIED TYPE; WATER; GLYCERIN

Drug Facts

ACTIVE INGREDIENT

Benzalkonium chloride 0.1%

PURPOSE

Antimicrobial

Uses

For hand sanitizing to decrease bacteria on the skin.

Recommended for repeated use.

WARNINGS

For external use only

When using this product avoid contact with eyes. In case of eye contact, flush eyes with water.

Stop use and ask a doctor if irritation or redness develops, or if condition persists for more than 72 hours.

Keep out of reach of children. If swallowed, get medical help or contact a Poison Control Center right away.

Directions

- Pump a small amount of gel into pal of hand
- Rub thoroughly over all surfaces of both hands
- Rub hands together briskly until dry.

INACTIVE INGREDIENT

Water, carbomer, glycerin, lactic acid.

PACKAGE LABEL

74146-244-02